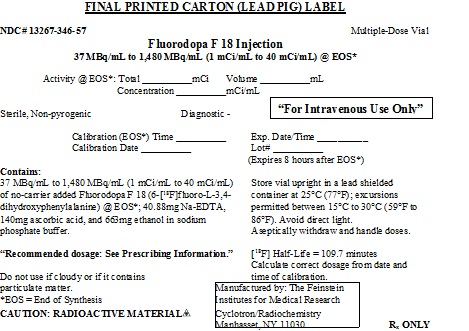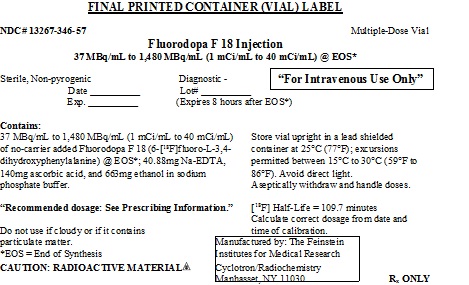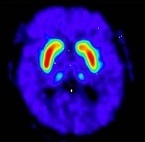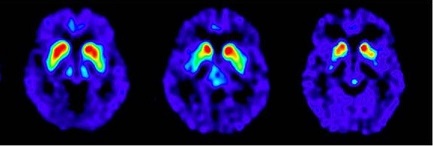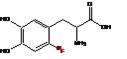 DRUG LABEL: Fluorodopa
NDC: 13267-346 | Form: INJECTION
Manufacturer: THE FEINSTEIN INSTITUTES FOR MEDICAL RESEARCH
Category: prescription | Type: HUMAN PRESCRIPTION DRUG LABEL
Date: 20210115

ACTIVE INGREDIENTS: FLUORODOPA F-18 40 mCi/1 mL
INACTIVE INGREDIENTS: EDETATE DISODIUM 1.46 mg/1 mL; ASCORBIC ACID 5 mg/1 mL; ALCOHOL 23.68 mg/1 mL

HIGHLIGHTS OF PRESCRIBING INFORMATION

These highlights do not include all the information needed to use FLUORODOPA F 18 Injection safely and effectively. See full prescribing information for FLUORODOPA F 18 Injection.
FLUORODOPA F 18 Injection, for intravenous use
Initial U.S. Approval: 2019

1 INDICATIONS AND USAGE

Fluorodopa F 18 Injection is a radioactive diagnostic agent indicated for use in positron emission tomography (PET) to visualize dopaminergic nerve terminals in the striatum for the evaluation of adult patients with suspected Parkinsonian syndromes (PS). Fluorodopa F 18 PET is an adjunct to other diagnostic evaluations.

2 DOSAGE AND ADMINISTRATION

• The recommended adult dose is 185 megabecquerels (MBq) [5 millicuries (mCi)] by intravenous injection infused over 1 minute. (2.2)
• Use aseptic techniques and radiation shielding to maintain sterility during all operations involved in the manipulation and administration of Fluorodopa F 18 Injection. (2.1, 2.2)
• Instruct patients to void immediately before imaging and start imaging at approximately 80 minutes post administration (with a 9 second CT scan for attenuation correction) followed by 3D PET scan from 80 to 100 minutes post administration. (2.5)
• See full prescribing information for additional preparation, administration, imaging and radiation dosimetry information. (2)

3 DOSAGE FORMS AND STRENGTHS

Injection: clear, colorless solution in a multiple-dose glass vial containing 37 MBq/mL to 1,480 MBq/mL (1 mCi/mL to 40 mCi/mL) of Fluorodopa F 18 Injection. (3)

4 CONTRAINDICATIONS

None

5 WARNINGS AND PRECAUTIONS

Radiation risks: Use smallest dose necessary for imaging and ensure safe handling to protect the patient and healthcare worker from radiation exposure. (5.1)

6 ADVERSE REACTIONS

Injection site pain occurred with administration based on a review of the published literature. (6.2)

To report SUSPECTED ADVERSE REACTIONS, contact The Feinstein Institutes for Medical Research at 516-562-1052 or FDA at 1-800-FDA-1088 or www.fda.gov/medwatch.

8 USE IN SPECIFIC POPULATIONS

• Lactation: To decrease radiation exposure to a nursing infant, advise a lactating woman to pump and discard breastmilk for at least 24 hours (12 half-lives) after administration of Fluorodopa F 18 Injection. (8.2)

FULL PRESCRIBING INFORMATION

1 INDICATIONS AND USAGE

Fluorodopa F 18 Injection is indicated for use in positron emission tomography (PET) to visualize dopaminergic nerve terminals in the striatum for the evaluation of adult patients with suspected Parkinsonian syndromes (PS). Fluorodopa F 18 PET is an adjunct to other diagnostic evaluations.

2 DOSAGE AND ADMINISTRATION

2.1 Radiation Safety - Drug Handling

• Handle Fluorodopa F 18 Injection with appropriate safety measures to minimize radiation exposure [see Warnings and Precautions (5.1)]. Use waterproof gloves, effective shielding and appropriate safety measures to avoid unnecessary radiation exposure to the patient, occupational workers, clinical personnel, and other persons.

2.2 Recommended Dosage and Administration

Recommended Dose
• The recommended dose for adults is 185 megabecquerels (MBq) [5 millicuries (mCi)] administered as an intravenous injection infused over 1 minute.
• Minimize the dose of Fluorodopa F 18 Injection consistent with the objectives of the procedure and the nature of the imaging cameras employed.

Administration
• Use aseptic techniques and radiation shielding during all operations involved in the manipulation and administration of Fluorodopa F 18 Injection.
• Calculate the necessary volume to administer based on calibration time and dose.
• Inspect Fluorodopa F 18 Injection visually and do not use the drug if the solution contains particulate matter or is discolored.
• Measure the patient dose immediately prior to administration in a dose calibrator.
• Dispose of unused drug in compliance with applicable regulations.

2.3 Patient Preparation

Hydration
• Patients must have nothing to eat or drink, except water for 4 hours before administration
• To minimize the radiation absorbed dose to the bladder, instruct patient to:
o hydrate 4 hours prior to the administration of Fluorodopa F 18 Injection and continue hydration after the study.
o void 70 minutes after administration of Fluorodopa F 18 Injection and as frequently thereafter as possible for the next 12 hours.

Pre-medication and Medication Withdrawal
• Carbidopa blocks systemic/peripheral decarboxylation of Fluorodopa F 18 Injection to increase uptake in the brain. Administer 150 mg of Carbidopa orally at least 60 minutes (and no longer than 120 minutes) prior to the administration of Fluorodopa F 18 Injection.
• Instruct the patient to discontinue medications for the treatment of Parkinson’s disease 12 hours prior to administration of Fluorodopa F 18 Injection [see Drug Interactions (7)].

2.4 Radiation Dosimetry

The estimated human absorbed radiation dose for 10 human subjects (8 men and 2 women; mean age 50 ±8.8 yr) from intravenous administration of Fluorodopa F 18 Injection is shown in Table 1. In subjects who voided at 40 min post-injection, the radiation absorbed dose to the bladder wall was 50% lower than the radiation absorbed dose in subjects who voided at 2 hours post-injection. The identified critical organ is the urinary bladder.

Table 1. Estimated Absorbed Radiation Dose (mGy/MBq) for Adult Patients after Intravenous Administration of Fluorodopa F 18 Injectiona
Organ | Absorbed Dose per unit activity (mGy/MBq)
Urinary bladder wall | 0.30
Heart wall | 0.01
Pancreas | 0.01
Spleen | 0.01
Lungs | 0.01
Kidneys | 0.03
Ovaries | 0.02
Uterus | 0.03
Lower Large Intestine wall | 0.02
Liver | 0.01
Gallbladder wall | 0.01
Small Intestine | 0.01
Upper Large Intestine wall | 0.01
Stomach wall | 0.01
Adrenals | 0.01
Testes | 0.01
Red marrow | 0.01
Thymus | 0.01
Thyroid | 0.01
Muscle | 0.01
Bone surfaces | 0.01
Breast | 0.01
Skin | 0.01
Brain | 0.01
Remaining organs | 0.01
Effective dose (mSv/MBq) | 0.03

aICRP Publication 128, Radiation Dose to Patients from Radiopharmaceuticals, Annals of the ICRP, Vol. 44, No. 2S, 2015.

2.5 Imaging Guidelines

• Instruct the patient to void immediately before imaging, 70 minutes post administration.
• Start imaging at about 80 minutes post administration (with a 9 second CT scan for attenuation correction) followed by 3D PET scan from 80 to 100 minutes post administration.

2.6 Image Interpretation

Fluorodopa F 18 PET scans are interpreted visually, based upon the appearance and shape of the putamen and caudate of the striatum. Optimum presentation of the reconstructed images for visual interpretation is transaxial slices parallel to the anterior commissure-posterior commissure (AC-PC) line. Determination of whether an image is negative or positive is made by assessing the shape and intensity of the striatal signal (see Figure 1 and 2). Image interpretation does not involve integration of the image with clinical signs and/or symptoms.

Negative Scans: A full crescent shaped putamen and caudate image (see Figure 1). FDOPA uptake is clearly delineated from the background activity in the brain. It is bilaterally symmetrical and of uniform thickness in both caudate and putamen (comma- or crescent-shaped).

Figure 1: Negative Scan

Positive Scans: A reduction in the size and shape of putamen (unilaterally or bilaterally) or both putamen and caudate (unilaterally or bilaterally). All of the following are considered positive:
• FDOPA uptake is asymmetric in the putamen; normal on one side but reduced on the contralateral side with respect to the background, especially in the posterior part. Caudate uptake is symmetrical on both sides and clearly delineated from the background (see Figure 2, A).
• FDOPA uptake is bilaterally reduced in the putamen (see Figure 2, B).
• FDOPA uptake is bilaterally reduced in the putamen and in the caudate nuclei (see Figure 2, C).

Figure 2: Positive Scans

A B C

3 DOSAGE FORMS AND STRENGTHS

Injection: clear, colorless solution containing 37 MBq/mL to 1,480 MBq/mL (1 mCi/mL to 40 mCi/mL) of Fluorodopa F 18 Injection, at calibration time in a multiple-dose glass vial.

4 CONTRAINDICATIONS

None

5 WARNINGS AND PRECAUTIONS

5.1 Radiation Risks

Fluorodopa F 18 Injection use contributes to a patient’s overall long-term radiation exposure, which is associated with an increased risk of cancer. Use the smallest dose necessary for imaging and ensure safe handling to protect the patient and health care worker [see Dosage and Administration (2.1, 2.2)].

6 ADVERSE REACTIONS

6.1 Clinical Trials Experience

Because clinical trials are conducted under widely varying conditions, adverse reaction rates observed in the clinical trials of a drug cannot be directly compared to rates in the clinical trials of another drug and may not reflect the rates observed in practice. No adverse reactions have been reported for Fluorodopa F 18 Injection based on an open-label clinical trial in 68 patients [see Clinical Studies (14)] and additional clinical experience in 53 patients.

6.2 Postmarketing Experience

The following adverse reactions have been identified during post approval of use of Fluorodopa F 18 Injection outside of the United States. Because these reactions are reported voluntarily from a population of uncertain size, it is not always possible to reliably estimate their frequency or establish a causal relationship to drug exposure.

General Disorders and Administration Site Conditions: Pain

7 DRUG INTERACTIONS

Aromatic L-amino acid decarboxylase (AADC) inhibitors
Prior to Fluorodopa F 18 Injection administration, use of AADC inhibitors (e.g. carbidopa, benserazide etc.) may increase Fluorodopa F 18 bioavailability to the brain by inhibiting peripheral decarboxylase activity and restricting peripheral Fluorodopa F 18 metabolism [see Dosage and Administration (2.3)].

Dopamine agonists, dopamine reuptake inhibitors, dopamine releasing agents (DRAs), peripheral catechol-O-methyltransferase (COMT) inhibitors, and monoamine oxidase (MAO) inhibitors
Therapy for Parkinson’s syndromes includes dopamine agonists, dopamine reuptake inhibitors, dopamine releasing agents (DRAs) such as psychostimulants of the amphetamine class, peripheral catechol-O-methyltransferase (COMT) inhibitors, and monoamine oxidase (MAO) inhibitors. Whether discontinuation of these drugs prior to Fluorodopa F 18 administration may minimize the interference with a Fluorodopa F 18 image is not fully known; however, if use of these drugs can be safely suspended, discontinue use 12 hours before administration of Fluorodopa F18 Injection [see Dosage and Administration (2.3)].

8 USE IN SPECIFIC POPULATIONS

8.1 Pregnancy

Risk Summary
There are no available data on Fluorodopa F 18 Injection use in pregnant women. Additionally, animal reproductive and developmental toxicity studies have not been conducted with Fluorodopa F 18 Injection. However, all radiopharmaceuticals, including Fluorodopa F 18 Injection, have a potential to cause fetal harm depending on the stage of fetal development, and the magnitude of the radiation dose. If considering Fluorodopa F 18 Injection administration to a pregnant woman, inform the patient about the potential for adverse pregnancy outcomes based on the radiation dose from the drug and the gestational timing of exposure.

The estimated background risk of major birth defects and miscarriage for the indicated population is unknown. All pregnancies have a background risk of birth defect, loss, or other adverse outcomes. In the U.S. general population, the estimated background risks of major birth defects and miscarriage in clinically recognized pregnancies are 2 to 4% and 15 to 20%, respectively, regardless of drug exposure.

8.2 Lactation

Risk Summary
No data are available regarding the presence of Fluorodopa F 18 Injection in human milk, the effects of the drug on the breastfed child, or the effects of the drug on milk production. Exposure of Fluorodopa F 18 Injection to a breast fed infant can be minimized by temporary discontinuation of breastfeeding [see Clinical Considerations]. The developmental and health benefits of breastfeeding should be considered along with the mother’s clinical need for Fluorodopa F 18 Injection and any potential adverse effects on the breastfed child from Fluorodopa F 18 Injection or from the underlying maternal condition.

The body of scientific information related to radioactivity decay, drug tissue distribution and drug elimination shows that less than 0.01% of the radioactivity administered remains in the body after 24 hours.

Clinical Considerations
To decrease radiation exposure to a nursing infant, advise a lactating woman to pump and discard breastmilk for at least 24 hours (12 half-lives) after administration of Fluorodopa F 18 Injection.

8.4 Pediatric Use

The safety and effectiveness of Fluorodopa F 18 Injection for visualization of dopaminergic neurons in the striatum has not been established in pediatric patients.

11 DESCRIPTION

11.1 Chemical Characteristics

Fluorodopa F 18 Injection is a radioactive diagnostic agent used in PET imaging. The active ingredient 6-[^18F] Fluoro-L-3, 4-dihydroxyphenylalanine has the molecular formula of C9H10FNO4 with a molecular weight of 214.18, and has the following chemical structure:

Fluorodopa F 18 Injection is a sterile, pyrogen-free, clear, colorless solution. Each mL contains between 37 MBq/mL to 1,480 MBq/mL (1 mCi/mL to 40 mCi/mL) of no-carrier added Fluorodopa F 18 (6-[^18F] Fluoro-L-3, 4-dihydroxyphenylalanine) at the end of synthesis (EOS). There is 40.88 mg Na-EDTA, 140 mg ascorbic acid, and 663 mg ethanol in 28 mL ±1 mL sodium phosphate buffer. The pH of the solution is between 3 and 5.

11.2 Physical Characteristics

Fluorine F 18 is a cyclotron produced radionuclide that decays by positron emission to Oxygen O 18 (stable) and has a physical half-life of 109.7 minutes. The principal photons useful for imaging are the dual 511 keV gamma photons, which are produced and emitted simultaneously in opposite direction following positron-electron annihilation (Table 2).

Table 2. Principal Radiation Emission Data for Fluoride F 18
Radiation/Emission | % Per Disintegration | Mean Energy
Positron(+) | 96.73 | 249.8 keV
Gamma(±)* | 193.46 | 511.0 keV

*Produced by positron annihilation

11.3 External Radiation

The point source air-kerma coefficient for F 18 is 3.75 × 10^-17 Gy m^2 / (Bq s). The half-value layer (HVL) for the 511 keV photons is 5 mm lead (Pb). The range of attenuation coefficients for this radionuclide as a function of lead shield thickness is shown in Table 3. For example, the interposition of a 9 mm thickness of Pb, with a coefficient of attenuation of 0.25, will decrease the external radiation by 75%.

Table 3. Radiation Attenuation of 511 keV Photons by lead (Pb) shielding
Shield thickness (Pb) mm | Coefficient of Attenuation
0 | 0.00
5 | 0.50
9 | 0.25
15 | 0.10
29 | 0.01
39 | 0.001
52 | 0.0001

For use in correcting for physical decay of this radionuclide, the fractions remaining at selected intervals after calibration are shown in Table 4.

Table 4. Physical Decay Chart for Fluorine F 18
Time Since Calibration | Fraction Remaining
0* | 1.000
15 min | 0.909
30 min | 0.826
60 min | 0.683
110 min | 0.500
220 min | 0.250
440 min | 0.060
12 hours | 0.011
24 hours | 0.0001

*Calibration time

12 CLINICAL PHARMACOLOGY

12.1 Mechanism of Action

In dopaminergic nerve terminals in the brain, Fluorodopa (FDOPA) F 18 is decarboxylated by amino acid decarboxylase to Fluorodopamine (FDA) F 18 and stored in presynaptic vesicles in the brain. The accumulation of F 18 FDA in the striatum is visually detected in the PET scan.

12.2 Pharmacodynamics

Optimal PET imaging is achieved between 75 to 90 minutes after administration of Fluorodopa F 18 Injection based on its pharmacokinetics. The relationship between Fluorodopa F 18 dose and plasma concentration is not fully characterized.

12.3 Pharmacokinetics

Distribution
Following the intravenous administration, Fluorodopa F 18 is cleared from the blood with a biologic half-life of about 1 to 3 hours. The time course of “background” brain radioactivity after Fluorodopa F 18 was evaluated. F 18 activity in the cerebellum was greater than the parietal or occipital cortex during the first 30 minutes after Fluorodopa F 18 suggesting regional differences in amino acid transport.

Elimination
Fluorodopa F 18 is cleared from the blood and tissue within 24 hours.

Metabolism: Fluorodopa F 18 is decarboxylated by aromatic amino acid decarboxylase in the striatum to Fluorodopamine F 18. Fluorodopamine F 18 is also metabolized via monoamine oxidase to yield [^18F] 6-fluoro-3,4-dihydroxyphenylacetic acid (^18FDOPAC) and subsequently by COMT to yield [^18F]6-fluorohomovanillic acid (^18FHVA).

Elimination: 80% of the radioactivity is eliminated through the urine. Urine radioactivity peaks at about 30 minutes post-injection. The radiation absorbed dose to the bladder wall is reduced by emptying the bladder just before scanning.

14 CLINICAL STUDIES

The safety and efficacy of F-18 FDOPA were evaluated in a prospective single-arm study conducted at a single center that enrolled 68 adult patients with possible Parkinsonian syndrome (PS). In the study, F-18 FDOPA image reads were compared to a reference clinical diagnostic standard of Parkinsonian syndrome or non-Parkinsonian syndrome (non-PS) established at 6 to 9 months after the F-18 FDOPA PET scan by a movement disorder specialist blinded to F-18 FDOPA PET results. The reference clinical diagnostic standard for PS included Parkinson's disease (PD), progressive supranuclear palsy (PSP), corticobasal degeneration (CBD), and multiple system atrophy (MSA). These conditions have been associated with dopaminergic neurodegeneration and F-18 FDOPA PET imaging was not designed to distinguish among the conditions. The reference clinical diagnostic standard for non-PS included essential tremor (ET) diagnosis, vascular parkinsonism, drug-induced parkinsonism, and other non-PS diagnoses.

Carbidopa (150 mg) was administered orally to patients approximately 60 minutes prior to the administration of Fluorodopa F 18 Injection. Each patient was injected 5 mCi F-18 FDOPA (range 4.5-5.5 mCi), and PET images were acquired 80-100 minutes post injection.

F-18 FDOPA PET images were evaluated independently by 3 readers blinded to clinical information who had no other role in patient assessment. Patients with at least one cardinal feature of PS were referred to the study by physicians who were uncertain of a diagnosis. Thirty-three of these patients had symptoms for 2 years or less. Fifty-six of these patients completed F-18 FDOPA PET imaging and at least 6 month clinical follow-up. Among these 56 patients, 32% were female and 68% were male. Mean patient age was 66 years. Thirty-three patients were categorized as PS, and twenty-three patients were categorized as non-PS based on minimum 6 month clinical follow-up by a movement disorder specialist.

Table 5 shows the positive percent agreement and negative percent agreement of F-18 FDOPA Injection PET image results with the reference clinical diagnostic standard. Positive percent agreement represents the percent of patients with positive F-18 FDOPA PET images among all the patients with a clinical diagnostic reference standard of PS. Negative percent agreement represents the percent of patients with negative F-18 FDOPA PET images among the patients with a non-PS clinical diagnostic reference standard.

Table 5. Positive and Negative Percent Agreement for F-18 FDOPA Injection PET Imaging
n=56 Patients | Positive percent agreement; Positive test/Clinical PS; (95 % CI) | Negative percent agreement; Negative test/Clinical non-PS; (95 % CI)
Reader 1 | 24/33; 73% (55, 87) | 21/23; 91% (72, 99)
Reader 2 | 16/33; 49% (31, 67) | 21/23; 91% (72, 99)
Reader 3 | 19/33; 58% (39, 75) | 19/23; 83% (61, 94)

The effectiveness of F-18 FDOPA PET as a screening or confirmatory test and for monitoring disease progression or response to therapy has not been established.

16 HOW SUPPLIED/STORAGE AND DRUG HANDLING

Fluorodopa F 18 Injection (NDC 13267-346-57) is supplied as a clear, colorless injection in a septum capped glass vial containing between 37 MBq/mL to 1,480 MBq/mL (1 mCi/mL to 40 mCi/mL), of Fluorodopa F 18 at calibration time, in 28 mL ±1 mL.

Storage
Store the Fluorodopa F 18 Injection vial upright in a lead shielded container at 25°C (77°F); excursions permitted between 15ºC to 30°C (59ºF to 86°F). Avoid direct light.

The expiration date and time are provided on the container label. Use Fluorodopa F 18 Injection within 8 hours from the time of the end of synthesis (EOS).

Handling
This radiopharmaceutical is for distribution and use by persons licensed authorized by the U.S. Nuclear Regulatory Commission or the relevant regulatory authority of an Agreement State. Store and dispose of Fluorodopa F 18 in compliance with the appropriate regulations of the government agency authorized to license the use of this radionuclide.

17 PATIENT COUNSELING INFORMATION

Patient Preparation
Instruct patients to:
• Drink water in the 4 hours before their PET study and continue hydration with water or other fluids (as tolerated) after the study.
• Void 70 minutes after the administration of Fluorodopa F 18, before the start of the imaging study, and as frequently as possible after the study is complete for a total of 12 hours [see Dosage and Administration (2.3)].

Lactation
To decrease radiation exposure to a nursing infant, advise a lactating woman to pump and discard breastmilk for at least 24 hours (12 half-lives) after administration of Fluorodopa F 18 Injection. (8.2)

Manufactured & Distributed by:
The Feinstein Institutes for Medical Research
Cyclotron/Radiochemistry Facility
350 Community Drive
Manhasset, New York 11030